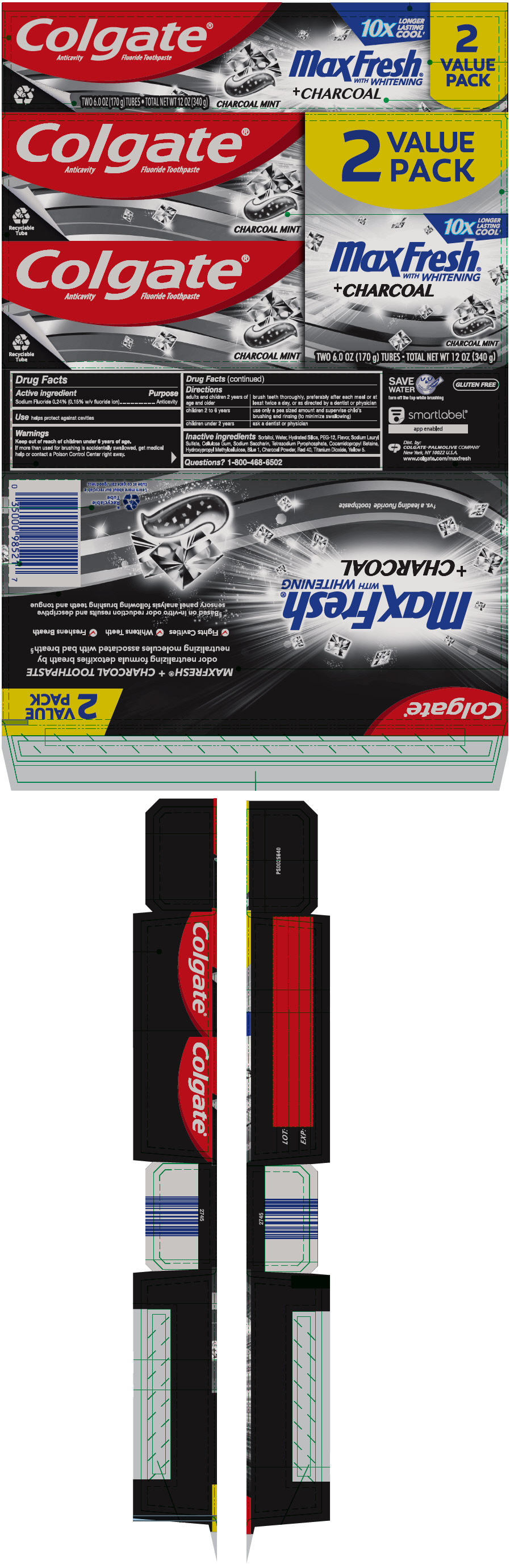 DRUG LABEL: Colgate MaxFresh Charcoal
NDC: 35000-990 | Form: GEL, DENTIFRICE
Manufacturer: Colgate-Palmolive Company
Category: otc | Type: HUMAN OTC DRUG LABEL
Date: 20251015

ACTIVE INGREDIENTS: SODIUM FLUORIDE 1.1 mg/1 g
INACTIVE INGREDIENTS: SORBITOL; WATER; HYDRATED SILICA; POLYETHYLENE GLYCOL 600; SODIUM LAURYL SULFATE; CARBOXYMETHYLCELLULOSE SODIUM, UNSPECIFIED; SACCHARIN SODIUM; SODIUM PYROPHOSPHATE; COCAMIDOPROPYL BETAINE; HYPROMELLOSE, UNSPECIFIED; FD&C BLUE NO. 1; ACTIVATED CHARCOAL; FD&C RED NO. 40; TITANIUM DIOXIDE; FD&C YELLOW NO. 5

Colgate® MaxFresh® Charcoal

Drug Facts

Active ingredient

Sodium Fluoride 0.24% (0.15% w/v fluoride ion)

Purpose

Anticavity

Use

helps protect against cavities

Warnings

Keep out of reach of children under 6 years of age.

If more than used for brushing is accidentally swallowed, get medical help or contact a Poison Control Center right away.

Directions

adults and children 2 years of age and older | brush teeth thoroughly, preferably after each meal or at least twice a day, or as directed by a dentist or physician
children 2 to 6 years | use only a pea sized amount and supervise child's brushing and rinsing (to minimize swallowing)
children under 2 years | ask a dentist or physician

Inactive ingredients

Sorbitol, Water, Hydrated Silica, PEG-12, Flavor, Sodium Lauryl Sulfate, Cellulose Gum, Sodium Saccharin, Tetrasodium Pyrophosphate, Cocamidopropyl Betaine, Hydroxypropyl Methylcellulose, Blue 1, Charcoal Powder, Red 40, Titanium Dioxide, Yellow 5.

Questions?

1-800-468-6502

Dist. by:
COLGATE-PALMOLIVE COMPANY
New York, NY 10022 U.S.A.

PRINCIPAL DISPLAY PANEL - Two 170 g Tube Carton

Colgate®
Anticavity Fluoride Toothpaste

Recyclable
Tube

CHARCOAL MINT

2
VALUE
PACK

10X
LONGER
LASTING
COOL†

MaxFresh®
WITH WHITENING
+ CHARCOAL

CHARCOAL MINT

TWO 6.0 OZ (170 g) TUBES • TOTAL NET WT 12 OZ (340 g)